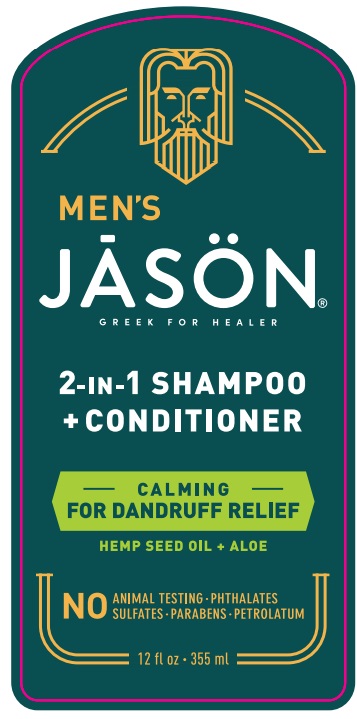 DRUG LABEL: Jason Dandruff Relief Treatment 2 in 1
NDC: 61995-0029 | Form: SHAMPOO
Manufacturer: The Hain Celestial Group, Inc
Category: otc | Type: HUMAN OTC DRUG LABEL
Date: 20240731

ACTIVE INGREDIENTS: PYRITHIONE ZINC 1 g/100 g
INACTIVE INGREDIENTS: WATER; SODIUM COCOYL ISETHIONATE; LAURYL GLUCOSIDE; GLYCERIN; SODIUM COCO-SULFATE; GLYCOL STEARATE; CETYL ALCOHOL; BABASSU OIL; OLIVE OIL; COCO GLUCOSIDE; GLYCERYL OLEATE; JOJOBA OIL; SODIUM PYRROLIDONE CARBOXYLATE; ZINC CARBONATE; POGOSTEMON CABLIN LEAF OIL; ALOE VERA LEAF; NUTMEG OIL; GINGER OIL; CANNABIS SATIVA SEED OIL; ANISE OIL; PEG-4 CAPRYLIC/CAPRIC GLYCERIDES; XANTHAN GUM; POTASSIUM SORBATE; HYDROGENATED SOYBEAN OIL; LEUCONOSTOC/RADISH ROOT FERMENT FILTRATE; CAPRYLOYL GLYCERIN/SEBACIC ACID COPOLYMER (2000 MPA.S); CITRIC ACID ACETATE; SODIUM HYDROXIDE; COCAMIDOPROPYL HYDROXYSULTAINE; SODIUM CHLORIDE; SHEA BUTTER; LEMON PEEL; CLOVE LEAF OIL; CANNABIS SATIVA SEED; ETHYLHEXYLGLYCERIN; LINALOOL, (+)-; BENZYL SALICYLATE; ALCOHOL 95%; ASCORBYL PALMITATE; ORANGE PEEL; MANDARIN OIL; JUNIPERUS OXYCEDRUS LEAF OIL; PELARGONIUM GRAVEOLENS FLOWER OIL; QUINOA OIL; DIHEPTYL SUCCINATE; PHENOXYETHANOL; HYDROXYPROPYL CELLULOSE (1600000 WAMW); LIMONENE, (+)-; GUAR HYDROXYPROPYLTRIMONIUM CHLORIDE (1.7 SUBSTITUENTS PER SACCHARIDE)

J04613 Jason Dandruff Relief Treatment 2 in 1
PF161810-02

ACTIVE INGREDIENT

Zinc Pyrithiopne 1.0%

PURPOSE

Controls Dandruff

INDICATIONS AND USAGE

- Controls recurrence of flaking, scaling and itching associated with dandruff
- Helps prevent seborrheic dermatitis

WARNINGS

For external use only .Avoid contact with eyes.Rinse eyes throughly with water in case contact occurs.Discontinue use and consult your physician if irritation develops.

Keep out of reach of children. If swallowed get medical help or contact Poison Center right away.

DOSAGE AND ADMINISTRATION

.

Gently massage a quarter-sized dollop onto wet scalp.
Leave on for 2-3 minutes.
Rinse throughly with tepid water.
For good results use every other day.
For maintenance use one or two treatment per week

Store between 40 to 100 degrees F (4 to 38 degrees C)

INACTIVE INGREDIENT

Water (Aqua), Sodium Cocoyl Isethionate, Glycerin, Cetyl Alcohol, Cocamidopropyl Hydroxysultaine, Sodium Cocoyl Glutamate, Sodium Laurylglucosides Hydroxypropylsulfonate, Sodium Chloride, Glyceryl Stearate SE, Coco-Glucoside, Glyceryl Oleate, Butyrospermum Parkii (Shea) Butter Unsaponifiables, Cannabis Sativa Seed Oil, Citrus Aurantium Dulcis (Orange) Peel Oil, Citrus Limon (Lemon) Peel Oil, Citrus Nobilis (Mandarin Orange) Peel Oil, Eugenia Caryophyllus (Clove) Leaf Oil, Juniperus Mexicana Oil, Myristica fragrans (Nutmeg) kernel oil, Olea Europaea (Olive) Fruit Oil (1), Pelargonium Graveolens Flower Oil, Pimpinella Anisum (Anise) Seed Oil, Pogostemon Cablin Oil, Simmondsia Chinensis (Jojoba) Seed Oil (1), Soybean Glycerides, Zingiber Officinale (Ginger) Root Oil, Aloe Barbadensis Leaf Juice (1), Cannabis Sativa Seed Extract, Chenopodium Quinoa Seed (1), Leuconostoc/Radish Root Ferment Filtrate, Ascorbyl Palmitate, Babassu Oil Polyglyceryl-4 Esters, Caprylic/Capric Triglyceride, Capryloyl Glycerin/Sebacic Acid Copolymer, Cellulose Gum, Citric Acid, Diheptyl Succinate, Guar Hydroxypropyltrimonium Chloride, Sodium Hydroxide, Sodium PCA, Xanthan Gum, Zinc Carbonate, Alcohol (1), Ethylhexylglycerin, Phenoxyethanol, Potassium Sorbate, Benzyl Salicylate, Fragrance (Natural), Limonene, Linalool.

(1) Certified Organic Ingredients

QUESTIONS

Questions?Visit www.jason-natural.com or call 1-877-527-Jason-01weekdays from 7am-5pm MST.